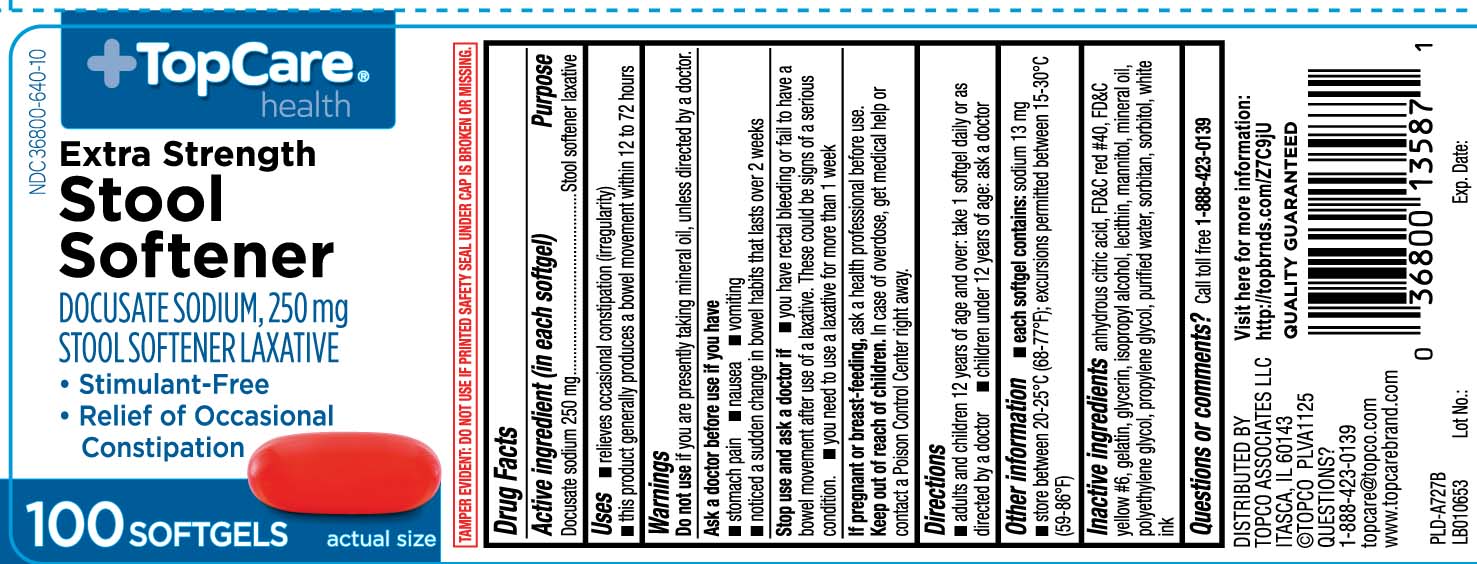 DRUG LABEL: Stool Softener
NDC: 36800-640 | Form: CAPSULE, LIQUID FILLED
Manufacturer: TOP CARE (Topco Associates LLC)
Category: otc | Type: HUMAN OTC DRUG LABEL
Date: 20260114

ACTIVE INGREDIENTS: DOCUSATE SODIUM 250 mg/1 1
INACTIVE INGREDIENTS: FD&C RED NO. 40; FD&C YELLOW NO. 6; GELATIN; GLYCERIN; POLYETHYLENE GLYCOL, UNSPECIFIED; PROPYLENE GLYCOL; WATER; SORBITOL; ANHYDROUS CITRIC ACID; ISOPROPYL ALCOHOL; LECITHIN, SOYBEAN; MANNITOL; MINERAL OIL; SORBITAN

Drug Facts

Active ingredient (in each softgel)

Docusate sodium 250 mg

Purpose

Stool softener laxative

Uses

- relieves occasional constipation (irregularity)
- this product generally produces a bowel movement within 12 to 72 hours

Warnings

Do not use

if you are presently taking mineral oil, unless directed by a doctor.

Ask a doctor before use if you have

- stomach pain
- nausea
- vomiting
- noticed a sudden change in bowel habits that last over 2 weeks

Stop use and ask a doctor if

- you have rectal bleeding or fail to have a bowel movement after use of a laxative. These could be signs of a serious condition.
- you need to use a laxative for more than 1 week

If pregnant or breast-feeding

ask a health professional before use.

Keep out of reach of children.

In case of overdose, get medical help or contact a Poison Control Center right away.

Directions

- adults and children 12 years of age and over: take 1 softgel daily or as directed by a doctor
- children under 12 years of age: ask a doctor

Other information

- each softgel contains: sodium 13 mg
- store between 20-25ºC (68-77ºF); excursions permitted between 15-30ºC (59-86ºF)

Inactive Ingredients

anhydrous citric acid, FD&C red #40, FD&C yellow #6, gelatin, glycerin, isopropyl alcohol, lecithin, mannitol, mineral oil, polyethylene glycol, propylene glycol, purified water, sorbitan, sorbitol, white ink

Questions or comments?

Call toll free 1-888-423-0139

Principal Display Panel

EXTRA STRENGTH

Stool Softener

DOCUSATE SODIUM, 250 mg

STOOL SOFTENER LAXATIVE

- Stimulant-free
- Relief of occasional constipation

SOFTGELS

TAMPER EVIDENT: DO NOT USE IF PRINTED SAFETY SEAL UNDER CAP IS BROKEN OR MISSING.

DISTRIBUTED BY

TOPCO ASSOCIATES LLC

ITASCA, IL 60143

Product Label

TOPCARE HEALTH Extra Strength Stool Softener